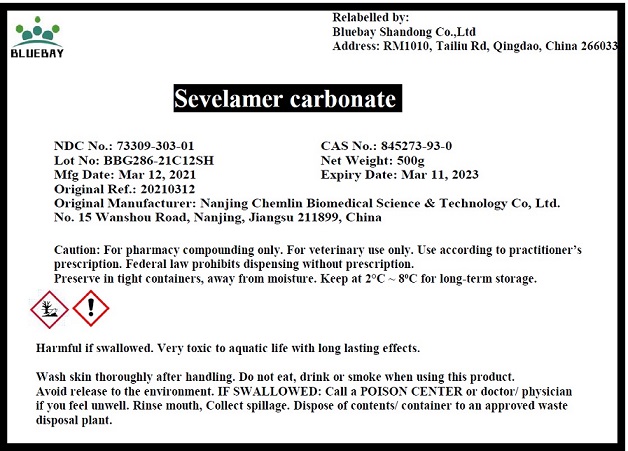 DRUG LABEL: Sevelamer Carbonate
NDC: 73309-303 | Form: POWDER
Manufacturer: Bluebay Shangdong Co.,LTD
Category: other | Type: BULK INGREDIENT
Date: 20210617

ACTIVE INGREDIENTS: Sevelamer Carbonate 1 g/1 g

Sevelamer Carbonate